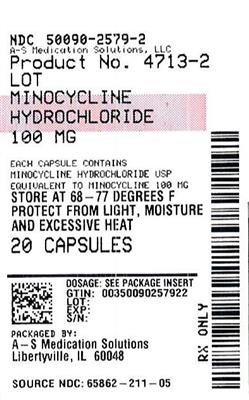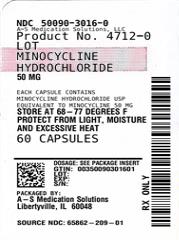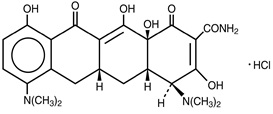 DRUG LABEL: Minocycline Hydrochloride
NDC: 50090-2579 | Form: CAPSULE
Manufacturer: A-S Medication Solutions
Category: prescription | Type: Human Prescription Drug Label
Date: 20260219

ACTIVE INGREDIENTS: MINOCYCLINE HYDROCHLORIDE 100 mg/1 1
INACTIVE INGREDIENTS: ZEA MAYS (CORN) STARCH; MAGNESIUM STEARATE; CI 77891; SODIUM LAURYL SULFATE; GELATIN; SHELLAC; DEHYDRATED ALCOHOL; ISOPROPYL ALCOHOL; BUTYL ALCOHOL; PROPYLENE GLYCOL; AMMONIA; CI 77499; POTASSIUM HYDROXIDE; BLUE 1; RED 28; RED 40; CI 77491

Minocycline Hydrochloride Capsules, USP
Rx only

To reduce the development of drug-resistant bacteria and maintain the effectiveness of minocycline hydrochloride capsules and other antibacterial drugs, minocycline hydrochloride capsules should be used only to treat or prevent infections that are proven or strongly suspected to be caused by bacteria.

DESCRIPTION

Minocycline hydrochloride, USP, is a semisynthetic derivative of tetracycline, 4,7-Bis(dimethylamino)-1,4,4a,5,5a,6,11,12a-octahydro-3,10,12,12a-tetrahydroxy-1,11-dioxo-2-naphthacenecarboxamide monohydrochloride.

Its structural formula is:

C23H27N3O7•HCl M.W. 493.94

Minocycline hydrochloride capsules, USP for oral administration contain minocycline hydrochloride, USP equivalent to 50 mg, 75 mg or 100 mg of minocycline. The capsule also contains the following inactive ingredients: corn starch and magnesium stearate. The empty hard gelatin capsule shells contain titanium dioxide, sodium lauryl sulfate, and gelatin. In addition, the 50 mg capsule shells contain FD&C Red #3, D&C Red #33, and FD&C Yellow #6; the 75 mg capsule shells contain black iron oxide; and the 100 mg capsule shells contain FD&C Blue #1, D&C Red #28, FD&C Red #40, and red iron oxide. The capsules are printed with edible ink containing shellac, dehydrated alcohol, isopropyl alcohol, butyl alcohol, propylene glycol, strong ammonia solution, black iron oxide, and potassium hydroxide.

CLINICAL PHARMACOLOGY

Following a single dose of two minocycline hydrochloride capsules, 100 mg administered to 18 normal fasting adult volunteers, maximum serum concentrations were attained in 1 to 4 hours (average 2.1 hours) and ranged from 2.1 to 5.1 mcg/mL (average 3.5 mcg/mL). The serum half-life in the normal volunteers ranged from 11.1 to 22.1 hours (average 15.5 hours).

When minocycline hydrochloride capsules were given concomitantly with a high-fat meal, which included dairy products, the extent of absorption of minocycline hydrochloride capsules was unchanged compared to dosing under fasting conditions. The mean Tmax was delayed by 1 hour when administered with food, compared to dosing under fasting conditions. Minocycline hydrochloride capsules may be administered with or without food.

In previous studies with other minocycline dosage forms, the minocycline serum half-life ranged from 11 to 16 hours in 7 patients with hepatic dysfunction, and from 18 to 69 hours in 5 patients with renal dysfunction. The urinary and fecal recovery of minocycline when administered to 12 normal volunteers was one-half to one-third that of other tetracyclines.

Microbiology

Mechanism of Action

The tetracyclines are primarily bacteriostatic and are thought to exert their antimicrobial effect by the inhibition of protein synthesis. The tetracyclines, including minocycline, have a similar antimicrobial spectrum of activity against a wide range of gram-positive and gram-negative organisms. Cross-resistance of these organisms to tetracycline is common.

Antimicrobial Activity

Minocycline has been shown to be active against most strains of the following microorganisms, both in vitro and in clinical infections (see INDICATIONS AND USAGE).

Gram-positive Bacteria

Bacillus anthracis

Listeria monocytogenes

Staphylococcus aureus

Streptococcus pneumoniae

Gram-negative Bacteria

Acinetobacter species

Bartonella bacilliformis

Brucella species

Campylobacter fetus

Escherichia coli

Francisella tularensis

Haemophilus ducreyi

Haemophilus influenzae

Klebsiella aerogenes

Klebsiella granulomatis

Klebsiella species

Neisseria gonorrhoeae

Neisseria meningitidis

Shigella species

Yersinia pestis

Vibrio cholerae

Other Microorganisms

Actinomyces species

Borrelia recurrentis

Chlamydophila psittaci

Chlamydia trachomatis

Clostridium species

Entamoeba species

Fusobacterium nucleatum subspecies fusiforme

Mycobacterium marinum

Mycoplasma pneumoniae

Propionibacterium acnes

Rickettsiae

Treponema pallidum subspecies pallidum

Treponema pallidum subspecies pertenue

Ureaplasma urealyticum

Susceptibility Testing

For specific information regarding susceptibility test interpretive criteria and associated test methods and quality control standards recognized by the FDA for this drug, please see https://www.fda.gov/STIC.

INDICATIONS AND USAGE

Minocycline hydrochloride capsules, USP are indicated in the treatment of the following infections due to susceptible strains of the designated microorganisms:

Rocky Mountain spotted fever, typhus fever and the typhus group, Q fever, rickettsialpox and tick fevers caused by rickettsiae.

Respiratory tract infections caused by Mycoplasma pneumoniae.

Lymphogranuloma venereum caused by Chlamydia trachomatis.

Psittacosis (Ornithosis) due to Chlamydophila psittaci.

Trachoma caused by Chlamydia trachomatis, although the infectious agent is not always eliminated, as judged by immunofluorescence.

Inclusion conjunctivitis caused by Chlamydia trachomatis.

Nongonococcal urethritis, endocervical, or rectal infections in adults caused by Ureaplasma urealyticum or Chlamydia trachomatis.

Relapsing fever due to Borrelia recurrentis.

Chancroid caused by Haemophilus ducreyi.

Plague due to Yersinia pestis.

Tularemia due to Francisella tularensis.

Cholera caused by Vibrio cholerae.

Campylobacter fetus infections caused by Campylobacter fetus.

Brucellosis due to Brucella species (in conjunction with streptomycin).

Bartonellosis due to Bartonella bacilliformis.

Granuloma inguinale caused by Klebsiella granulomatis.

Minocycline is indicated for the treatment of infections caused by the following gram-negative microorganisms when bacteriologic testing indicates appropriate susceptibility to the drug:

Escherichia coli.

Klebsiella aerogenes

Shigella species.

Acinetobacter species.

Respiratory tract infections caused by Haemophilus influenzae.

Respiratory tract and urinary tract infections caused by Klebsiella species.

Minocycline hydrochloride capsules, USP are indicated for the treatment of infections caused by the following gram-positive microorganisms when bacteriologic testing indicates appropriate susceptibility to the drug:

Upper respiratory tract infections caused by Streptococcus pneumoniae.

Skin and skin structure infections caused by Staphylococcus aureus. (NOTE: Minocycline is not the drug of choice in the treatment of any type of staphylococcal infection.)

When penicillin is contraindicated, minocycline is an alternative drug in the treatment of the following infections:

Uncomplicated urethritis in men due to Neisseria gonorrhoeae and for the treatment of other gonococcal infections.

Infections in women caused by Neisseria gonorrhoeae.

Syphilis caused by Treponema pallidum subspecies pallidum.

Yaws caused by Treponema pallidum subspecies pertenue.

Listeriosis due to Listeria monocytogenes.

Anthrax due to Bacillus anthracis.

Vincent's infection caused by Fusobacterium fusiforme.

Actinomycosis caused by Actinomyces israelii.

Infections caused by Clostridium species.

In acute intestinal amebiasis, minocycline may be a useful adjunct to amebicides.

In severe acne, minocycline may be useful adjunctive therapy.

Oral minocycline is indicated in the treatment of asymptomatic carriers of Neisseria meningitidis to eliminate meningococci from the nasopharynx. In order to preserve the usefulness of minocycline in the treatment of asymptomatic meningococcal carriers, diagnostic laboratory procedures, including serotyping and susceptibility testing, should be performed to establish the carrier state and the correct treatment. It is recommended that the prophylactic use of minocycline be reserved for situations in which the risk of meningococcal meningitis is high.

Oral minocycline is not indicated for the treatment of meningococcal infection.

Although no controlled clinical efficacy studies have been conducted, limited clinical data show that oral minocycline hydrochloride has been used successfully in the treatment of infections caused by Mycobacterium marinum.

To reduce the development of drug-resistant bacteria and maintain the effectiveness of minocycline hydrochloride capsules, USP and other antibacterial drugs, minocycline hydrochloride capsules, USP should be used only to treat or prevent infections that are proven or strongly suspected to be caused by susceptible bacteria. When culture and susceptibility information are available, they should be considered in selecting or modifying antibacterial therapy. In the absence of such data, local epidemiology and susceptibility patterns may contribute to the empiric selection of therapy.

CONTRAINDICATIONS

This drug is contraindicated in persons who have shown hypersensitivity to any of the tetracyclines or to any of the components of the product formulation.

WARNINGS

Tooth Development

Minocycline hydrochloride, like other tetracycline-class antibiotics, can cause fetal harm when administered to a pregnant woman. If any tetracycline is used during pregnancy or if the patient becomes pregnant while taking these drugs, the patient should be apprised of the potential hazard to the fetus. The use of drugs of the tetracycline class during tooth development (last half of pregnancy, infancy, and childhood to the age of 8 years) may cause permanent discoloration of the teeth (yellow-gray-brown).

This adverse reaction is more common during long-term use of the drug but has been observed following repeated short-term courses. Enamel hypoplasia has also been reported. Tetracycline drugs, therefore, should not be used during tooth development unless other drugs are not likely to be effective or are contraindicated.

Skeletal Development

All tetracyclines form a stable calcium complex in any bone-forming tissue. A decrease in the fibula growth rate has been observed in premature human infants given oral tetracycline in doses of 25 mg/kg every six hours. This reaction was shown to be reversible when the drug was discontinued.

Use in Pregnancy

Results of animal studies indicate that tetracyclines cross the placenta, are found in fetal tissues, and can have toxic effects on the developing fetus (often related to retardation of skeletal development). Evidence of embryotoxicity has been noted in animals treated early in pregnancy. The safety of minocycline hydrochloride for use during pregnancy has not been established.

Dermatologic Reaction

Drug Reaction with Eosinophilia and Systemic Symptoms (DRESS) including fatal cases has been reported with minocycline use. Fixed drug eruptions have occurred with minocycline and other tetracyclines. Worsening severity upon subsequent administrations, including generalized bullous fixed drug eruption, has been observed with other tetracyclines (see ADVERSE REACTIONS). If severe skin reactions occur, discontinue minocycline hydrochloride immediately and institute appropriate therapy.

Antianabolic Action

The antianabolic action of the tetracyclines may cause an increase in blood urea nitrogen (BUN). While this is not a problem in those with normal renal function, in patients with significantly impaired function, higher serum levels of tetracycline may lead to azotemia, hyperphosphatemia, and acidosis. Under such conditions, monitoring of creatinine and BUN is recommended, and the total daily dosage should not exceed 200 mg in 24 hours (see DOSAGE AND ADMINISTRATION). If renal impairment exists, even usual oral or parenteral doses may lead to systemic accumulation of the drug and possible liver toxicity.

Photosensitivity

Photosensitivity manifested by an exaggerated sunburn reaction has been observed in some individuals taking tetracyclines. This has been reported with minocycline.

Central Nervous System

Central nervous system side effects including lightheadedness, dizziness, or vertigo have been reported with minocycline therapy. Patients who experience these symptoms should be cautioned about driving vehicles or using hazardous machinery while on minocycline therapy. These symptoms may disappear during therapy and usually disappear rapidly when the drug is discontinued.

Clostridium difficile-Associated Diarrhea

Clostridium difficile-associated diarrhea (CDAD) has been reported with use of nearly all antibacterial agents, including minocycline hydrochloride, and may range in severity from mild diarrhea to fatal colitis. Treatment with antibacterial agents alters the normal flora of the colon leading to overgrowth of C. difficile.

C. difficile produces toxins A and B which contribute to the development of CDAD. Hypertoxin- producing strains of C. difficile cause increased morbidity and mortality, as these infections can be refractory to antimicrobial therapy and may require colectomy. CDAD must be considered in all patients who present with diarrhea following antibiotic use. Careful medical history is necessary since CDAD has been reported to occur over two months after the administration of antibacterial agents.

If CDAD is suspected or confirmed, ongoing antibiotic use not directed against C. difficile may need to be discontinued. Appropriate fluid and electrolyte management, protein supplementation, antibiotic treatment of C. difficile, and surgical evaluation should be instituted as clinically indicated.

Intracranial Hypertension

Intracranial hypertension (IH, pseudotumor cerebri) has been associated with the use of tetracyclines including minocycline hydrochloride. Clinical manifestations of IH include headache, blurred vision, diplopia, and vision loss; papilledema can be found on fundoscopy. Women of childbearing age who are overweight or have a history of IH are at greater risk for developing tetracycline-associated IH. Concomitant use of isotretinoin and minocycline hydrochloride should be avoided because isotretinoin is also known to cause pseudotumor cerebri.

Although IH typically resolves after discontinuation of treatment, the possibility for permanent visual loss exists. If visual disturbance occurs during treatment, prompt ophthalmologic evaluation is warranted. Since intracranial pressure can remain elevated for weeks after drug cessation, patients should be monitored until they stabilize.

PRECAUTIONS

General

As with other antibiotic preparations, use of this drug may result in overgrowth of non-susceptible organisms, including fungi. If superinfection occurs, the antibiotic should be discontinued, and appropriate therapy instituted.

Hepatotoxicity has been reported with minocycline; therefore, minocycline should be used with caution in patients with hepatic dysfunction and in conjunction with other hepatotoxic drugs.

Incision and drainage or other surgical procedures should be performed in conjunction with antibiotic therapy when indicated.

Prescribing minocycline hydrochloride capsules in the absence of a proven or strongly suspected bacterial infection or a prophylactic indication is unlikely to provide benefit to the patient and increases the risk of the development of drug-resistant bacteria.

Information for Patients

Diarrhea is a common problem caused by antibiotics which usually ends when the antibiotic is discontinued. Sometimes after starting treatment with antibiotics, patients can develop watery and bloody stools (with or without stomach cramps and fever) even as late as two or more months after having taken the last dose of the antibiotic. If this occurs, patients should contact their physician as soon as possible.

Photosensitivity manifested by an exaggerated sunburn reaction has been observed in some individuals taking tetracyclines. Patients apt to be exposed to direct sunlight or ultraviolet light should be advised that this reaction can occur with tetracycline drugs, and treatment should be discontinued at the first evidence of skin erythema. This reaction has been reported with use of minocycline.

Patients who experience central nervous system symptoms should be cautioned about driving vehicles or using hazardous machinery while on minocycline therapy (see WARNINGS).

Concurrent use of tetracycline with oral contraceptives may render oral contraceptives less effective (see PRECAUTIONS - Drug Interactions).

Patients should be counseled that antibacterial drugs including minocycline hydrochloride capsules should only be used to treat bacterial infections. They do not treat viral infections (e.g., the common cold). When minocycline hydrochloride capsules are prescribed to treat a bacterial infection, patients should be told that although it is common to feel better early in the course of therapy, the medication should be taken exactly as directed. Skipping doses or not completing the full course of therapy may (1) decrease the effectiveness of the immediate treatment and (2) increase the likelihood that bacteria will develop resistance and will not be treatable by minocycline hydrochloride capsules or other antibacterial drugs in the future.

Unused supplies of tetracycline antibiotics should be discarded by the expiration date.

Laboratory Tests

In venereal disease when coexistent syphilis is suspected, a dark-field examination should be done before treatment is started and the blood serology repeated monthly for at least four months.

Periodic laboratory evaluations of organ systems, including hematopoietic, renal, and hepatic, should be performed.

Drug Interactions

Because tetracyclines have been shown to depress plasma prothrombin activity, patients who are on anticoagulant therapy may require downward adjustment of their anticoagulant dosage.

Since bacteriostatic drugs may interfere with the bactericidal action of penicillin, it is advisable to avoid giving tetracycline-class drugs in conjunction with penicillin.

Absorption of tetracyclines is impaired by antacids containing aluminum, calcium, or magnesium, and iron-containing preparations.

Concurrent use of tetracyclines with oral contraceptives may render oral contraceptives less effective.

Administration of isotretinoin should be avoided shortly before, during, and shortly after minocycline therapy. Each drug alone has been associated with pseudotumor cerebri (see WARNINGS).

Increased risk of ergotism when ergot alkaloids or their derivatives are given with tetracyclines.

Drug/Laboratory Test Interactions

False elevations of urinary catecholamine levels may occur due to interference with the fluorescence test.

Carcinogenesis, Mutagenesis, Impairment of Fertility

Dietary administration of minocycline in long-term tumorigenicity studies in rats resulted in evidence of thyroid tumor production. Minocycline has also been found to produce thyroid hyperplasia in rats and dogs. In addition, there has been evidence of oncogenic activity in rats in studies with a related antibiotic, oxytetracycline (i.e., adrenal and pituitary tumors). Likewise, although mutagenicity studies of minocycline have not been conducted, positive results in in vitro mammalian cell assays (i.e., mouse lymphoma and Chinese hamster lung cells) have been reported for related antibiotics (tetracycline hydrochloride and oxytetracycline). Segment I (fertility and general reproduction) studies have provided evidence that minocycline impairs fertility in male rats.

Pregnancy

Risk Summary

All pregnancies have a background risk of birth defects, loss, or other adverse outcome regardless of drug exposure. There are no adequate and well-controlled studies on the use of minocycline in pregnant women. Minocycline, like other tetracycline-class antibiotics, crosses the placenta and may cause fetal harm when administered to a pregnant woman. Rare spontaneous reports of congenital anomalies including limb reduction have been reported in postmarketing experience. Only limited information is available regarding these reports; therefore, no conclusion on causal association can be established. If minocycline is used during pregnancy or if the patient becomes pregnant while taking this drug, the patient should be apprised of the potential hazard to the fetus.

Nonteratogenic Effects: (see WARNINGS.)

Labor and Delivery

The effect of tetracyclines on labor and delivery is unknown.

Nursing Mothers

Tetracyclines are excreted in human milk. Because of the potential for serious adverse reactions in nursing infants from the tetracyclines, a decision should be made whether to discontinue nursing or discontinue the drug, taking into account the importance of the drug to the mother (see WARNINGS).

Pediatric Use

Minocycline is not recommended for the use in children below 8 years of age unless the expected benefits of therapy outweigh the risks (see WARNINGS).

Geriatric Use

Clinical studies of oral minocycline did not include sufficient numbers of subjects aged 65 and over to determine whether they respond differently from younger subjects. In general, dose selection for an elderly patient should be cautious, usually starting at the low end of the dosing range, reflecting the greater frequency of decreased hepatic, renal, or cardiac function, and of concomitant disease or other drug therapy (see WARNINGS and DOSAGE AND ADMINISTRATION).

ADVERSE REACTIONS

Due to oral minocycline's virtually complete absorption, side effects to the lower bowel, particularly diarrhea, have been infrequent. The following adverse reactions have been observed in patients receiving tetracyclines:

Body as a whole: Fever and discoloration of secretions.

Gastrointestinal: Anorexia, nausea, vomiting, diarrhea, dyspepsia, stomatitis, glossitis, dysphagia, enamel hypoplasia, enterocolitis, pseudomembranous colitis, pancreatitis, inflammatory lesions (with monilial overgrowth) in the oral and anogenital regions. Instances of esophagitis and esophageal ulcerations have been reported in patients taking the tetracycline-class antibiotics in capsule and tablet form. Most of these patients took the medication immediately before going to bed (see DOSAGE AND ADMINISTRATION).

Genitourinary: Vulvovaginitis.

Hepatic toxicity: Hyperbilirubinemia, hepatic cholestasis, increases in liver enzymes, fatal hepatic failure, and jaundice. Hepatitis, including autoimmune hepatitis, and liver failure have been reported (see PRECAUTIONS).

Skin: Alopecia, erythema nodosum, hyperpigmentation of nails, pruritus, toxic epidermal necrolysis, vasculitis, maculopapular rash and erythematous rash. Exfoliative dermatitis has been reported. Fixed drug eruptions have been reported. Lesions occurring on the glans penis have caused balanitis. Erythema multiforme and Stevens-Johnson syndrome have been reported. Photosensitivity is discussed above (see WARNINGS-Photosensitivity). Pigmentation of the skin and mucous membranes has been reported.
Respiratory: Cough, dyspnea, bronchospasm, exacerbation of asthma, and pneumonitis.

Renal toxicity: Interstitial nephritis. Elevations in BUN have been reported and are apparently dose related (see WARNINGS). Reversible acute renal failure has been reported.

Musculoskeletal: Arthralgia, arthritis, bone discoloration, myalgia, joint stiffness, and joint swelling.

Hypersensitivity reactions: Urticaria, angioneurotic edema, polyarthralgia, anaphylaxis/anaphylactoid reaction (including shock and fatalities), anaphylactoid purpura, myocarditis, pericarditis, exacerbation of systemic lupus erythematosus and pulmonary infiltrates with eosinophilia have been reported. A transient lupus-like syndrome and serum sickness-like reactions also have been reported.

Blood: Agranulocytosis, hemolytic anemia, thrombocytopenia, leukopenia, neutropenia, pancytopenia, and eosinophilia have been reported.

Central Nervous System: Convulsions, dizziness, hypesthesia, paresthesia, sedation, and vertigo. Bulging fontanels in infants and benign intracranial hypertension (pseudotumor cerebri) in adults have been reported (see WARNINGS-Intracranial Hypertension). Headache has also been reported.

Other: Thyroid cancer has been reported in the postmarketing setting in association with minocycline products. When minocycline therapy is given over prolonged periods, monitoring for signs of thyroid cancer should be considered. When given over prolonged periods, tetracyclines have been reported to produce brown-black microscopic discoloration of the thyroid gland. Cases of abnormal thyroid function have been reported.

Tooth discoloration in children less than 8 years of age (see WARNINGS-Tooth Development) and also in adults has been reported.

Oral cavity discoloration (including tongue, lip, and gum) has been reported.

Tinnitus and decreased hearing have been reported in patients on minocycline hydrochloride.

The following syndromes have been reported. In some cases, involving these syndromes, death has been reported. As with other serious adverse reactions, if any of these syndromes are recognized, the drug should be discontinued immediately:

Hypersensitivity syndrome consisting of cutaneous reaction (such as rash or exfoliative dermatitis), eosinophilia, and one or more of the following: hepatitis, pneumonitis, nephritis, myocarditis, and pericarditis. Fever and lymphadenopathy may be present.

Lupus-like syndrome consisting of positive antinuclear antibody; arthralgia, arthritis, joint stiffness, or joint swelling; and one or more of the following: fever, myalgia, hepatitis, rash, and vasculitis.

Serum sickness-like syndrome consisting of fever; urticaria or rash; and arthralgia, arthritis, joint stiffness, or joint swelling and lymphadenopathy. Eosinophilia may be present.

Post-Marketing Experience

The following adverse reaction has been identified during post-approval use of minocycline products when taken orally. Because this reaction is reported voluntarily from a population of uncertain size, it is not always possible to reliably estimate their frequency or establish a causal relationship to drug exposure.

Skin and hypersensitivity reactions: Acute febrile neutrophilic dermatosis (Sweet’s syndrome).

To report SUSPECTED ADVERSE REACTIONS, contact Aurobindo Pharma USA, Inc. at 1-866-850-2876 or FDA at 1-800-FDA-1088 or www.fda.gov/medwatch.

OVERDOSAGE

The adverse events more commonly seen in overdose are dizziness, nausea, and vomiting.

No specific antidote for minocycline is known.

In case of overdosage, discontinue medication, treat symptomatically, and institute supportive measures. Minocycline is not removed in significant quantities by hemodialysis or peritoneal dialysis.

DOSAGE AND ADMINISTRATION

THE USUAL DOSAGE AND FREQUENCY OF ADMINISTRATION OF MINOCYCLINE DIFFER FROM THAT OF THE OTHER TETRACYCLINES. EXCEEDING THE RECOMMENDED DOSAGE MAY RESULT IN AN INCREASED INCIDENCE OF SIDE EFFECTS.

Minocycline hydrochloride capsules may be taken with or without food (see CLINICAL PHARMACOLOGY).

Ingestion of adequate amounts of fluids along with capsule and tablet forms of drugs in the tetracycline-class is recommended to reduce the risk of esophageal irritation and ulceration. The capsules should be swallowed whole.
For Pediatric Patients above 8 Years of Age
Usual pediatric dose: 4 mg/kg initially followed by 2 mg/kg every 12 hours, not to exceed the usual adult dose.

Adults

The usual dosage of minocycline hydrochloride capsules is 200 mg initially followed by 100 mg every 12 hours. Alternatively, if more frequent doses are preferred, two or four 50 mg capsules may be given initially followed by one 50 mg capsule 4 times daily.

Uncomplicated gonococcal infections other than urethritis and anorectal infections in men: 200 mg initially, followed by 100 mg every 12 hours for a minimum of 4 days, with post-therapy cultures within 2 to 3 days.

In the treatment of uncomplicated gonococcal urethritis in men, 100 mg every 12 hours for 5 days is recommended.

For the treatment of syphilis, the usual dosage of minocycline hydrochloride should be administered over a period of 10 to 15 days. Close follow-up, including laboratory tests, is recommended.

In the treatment of meningococcal carrier state, the recommended dosage is 100 mg every 12 hours for 5 days.

Mycobacterium marinum infections: Although optimal doses have not been established, 100 mg every 12 hours for 6 to 8 weeks have been used successfully in a limited number of cases.

Uncomplicated urethral, endocervical, or rectal infection in adults caused by Chlamydia trachomatis or Ureaplasma urealyticum: 100 mg orally, every 12 hours for at least 7 days.

Ingestion of adequate amounts of fluids along with capsule and tablet forms of drugs in the tetracycline class is recommended to reduce the risk of esophageal irritation and ulceration.

The pharmacokinetics of minocycline in patients with renal impairment (CLCR <80 mL/min) have not been fully characterized. Current data are insufficient to determine if a dosage adjustment is warranted. The total daily dosage should not exceed 200 mg in 24 hours. However, due to the antianabolic effect of tetracyclines, BUN and creatinine should be monitored (see WARNINGS-Antianabolic Action).

HOW SUPPLIED

Product: 50090-2579

NDC: 50090-2579-0 60 CAPSULE in a BOTTLE

NDC: 50090-2579-2 20 CAPSULE in a BOTTLE

NDC: 50090-2579-3 30 CAPSULE in a BOTTLE

NDC: 50090-2579-4 90 CAPSULE in a BOTTLE

Product: 50090-3016

NDC: 50090-3016-3 90 CAPSULE in a BOTTLE

NDC: 50090-3016-0 60 CAPSULE in a BOTTLE

ANIMAL PHARMACOLOGY AND TOXICOLOGY

Minocycline hydrochloride has been observed to cause a dark discoloration of the thyroid in experimental animals (rats, minipigs, dogs, and monkeys). In the rat, chronic treatment with minocycline hydrochloride has resulted in goiter accompanied by elevated radioactive iodine uptake and evidence of thyroid tumor production. Minocycline hydrochloride has also been found to produce thyroid hyperplasia in rats and dogs.
Distributed by:

Aurobindo Pharma USA, Inc.

279 Princeton-Hightstown Road

East Windsor, NJ 08520

Manufactured by:

Aurobindo Pharma Limited

Hyderabad-500 032, India

Revised: 04/2025

PATIENT INFORMATION
Minocycline Hydrochloride (min'' oh sye' kleen hye'' droe klor' ide)
Capsules, USP

Read the Patient Information that comes with minocycline hydrochloride capsules before you or a family member starts taking it and each time you get a refill. There may be new information. This Patient Information leaflet does not take the place of talking to your healthcare provider about your medical condition or treatment.

What are minocycline hydrochloride capsules?
Minocycline hydrochloride capsules are a tetracycline-class antibiotic medicine. Minocycline hydrochloride capsules are used to treat certain infections caused by bacteria. These include infections of the skin, respiratory tract, urinary tract, some sexually transmitted diseases, and others. Minocycline hydrochloride capsules may be used along with other treatments for severe acne.
Sometimes other germs, called viruses, cause infections. The common cold is a virus. Minocycline hydrochloride capsules, like other antibiotics, does not treat viruses.

Who should not take minocycline hydrochloride capsules?
Do not take minocycline hydrochloride capsules if you are allergic to minocycline or other tetracycline antibiotics.
Ask your doctor or pharmacist for a list of these medicines if you are not sure. See the end of this Patient Information leaflet for a complete list of ingredients in minocycline hydrochloride capsules.
Minocycline hydrochloride capsules are not recommended for pregnant women or children under 8 years of age because:
1. Minocycline hydrochloride capsules may harm an unborn baby.
2. Minocycline hydrochloride capsules may permanently turn a baby's or child's teeth yellow-gray-brown during tooth development. Tooth development happens in the last half of pregnancy and birth to age 8 years.

What should I tell my doctor before taking minocycline hydrochloride capsules?
Before taking minocycline hydrochloride capsules, tell your doctor about all of your medical conditions, including if you:

- have liver or kidney problems.
- are pregnant or plan to become pregnant. Minocycline hydrochloride capsules may harm your unborn baby. Stop taking minocycline hydrochloride capsules and call your doctor if you become pregnant while taking it.
- are breastfeeding or plan to breastfeed. Minocycline passes into your breast milk and may harm your baby. You and your doctor should decide if you will take minocycline hydrochloride capsules or breastfeed. You should not do both.

Tell your doctor about all the medicines you take, including prescription and over-the-counter medicines, vitamins, and herbal supplements. Using minocycline hydrochloride capsules with other medicines can cause side effects.
Especially tell your doctor if you take:

- birth control pills. Minocycline hydrochloride capsules may make your birth control pills less effective.
- a blood thinner medicine. The dose of your blood thinner may have to be lowered.
- a penicillin antibiotic medicine. Minocycline hydrochloride capsules and penicillins should not be used together.
- migraine medicines called ergot alkaloids.
- an acne medicine by mouth called isotretinoin.
- antacids that contain aluminum, calcium, or magnesium, or iron-containing products.

Know the medicines you take, keep a list of them to show your doctor and pharmacist each time you get a new medicine.

How should I take minocycline hydrochloride capsules?

- Take minocycline hydrochloride capsules exactly as your doctor tells you to take them. Skipping doses or not taking all your minocycline hydrochloride capsules may:
  - Decrease the effectiveness of the treatment.
  - Increase the chance that bacteria will develop resistance to minocycline hydrochloride capsules.
- Take minocycline hydrochloride capsules with a full glass of liquid. Taking minocycline hydrochloride capsules with enough liquid may lower your chance of getting irritation or ulcers in your esophagus. Your esophagus is the tube that connects your mouth to your stomach.
- Minocycline hydrochloride capsules may be taken with or without food. If you forget to take minocycline hydrochloride capsules, take it as soon as you remember.
- If you take too much minocycline hydrochloride, call your doctor or poison control center right away.

What are the possible side effects of minocycline hydrochloride capsules?
Minocycline hydrochloride capsules may cause serious side effects. Stop minocycline hydrochloride capsules and call your doctor if you have:

- watery diarrhea
- bloody stools
- stomach cramps
- unusual headaches
- blurred vision
- fever
- rash
- joint pain
- feeling very tired
- swollen lymph nodes

Minocycline hydrochloride capsules may also cause:

- central nervous system effects. Symptoms include light-headedness, dizziness, and a spinning feeling (vertigo). You should not drive or operate machines if you have these symptoms.
- sun sensitivity (photosensitivity). You may get a worse sunburn with minocycline hydrochloride capsules. Avoid sun exposure and the use of sunlamps or tanning beds. Protect your skin while out in the sunlight. Stop minocycline hydrochloride capsules and call your doctor if your skin turns red.

These are not all the possible side effects of minocycline hydrochloride capsules. For more information ask your doctor or pharmacist.
Call your doctor for medical advice about side effects. You may report side effects to FDA at 1-800-FDA-1088.

How should I store minocycline hydrochloride capsules?

- Store minocycline hydrochloride capsules at room temperature between 20° to 25°C (68° to 77°F).
- Keep minocycline hydrochloride capsules away from light, moisture, and excess heat.
- Throw away any minocycline hydrochloride capsules that is outdated or no longer needed.
- Keep minocycline hydrochloride capsules and all medicines out of the reach of children.

General information about the safe and effective use of minocycline hydrochloride capsules.
Medicines are sometimes prescribed for purposes other than those listed in a Patient Information leaflet. Do not take minocycline hydrochloride capsules for a condition for which it was not prescribed. Do not give minocycline hydrochloride capsules to other people, even if they have the same symptoms you have. It may harm them.
This Patient Information leaflet summarizes the most important information about minocycline hydrochloride capsules. If you would like more information, talk with your doctor. You can ask your doctor or pharmacist for information about minocycline hydrochloride capsules that is written for health professionals.
For more information, you can also call Aurobindo Pharma USA, Inc. at 1-866-850-2876.

What are the ingredients in minocycline hydrochloride capsules?
Active ingredient: minocycline hydrochloride USP, 50 mg, 75 mg and 100 mg
Inactive ingredients: Corn starch and magnesium stearate. The empty hard gelatin capsule shells contain titanium dioxide, sodium lauryl sulfate, and gelatin. In addition, the 50 mg capsule shells contain FD&C Red #3, D&C Red #33, and FD&C Yellow #6; the 75 mg capsule shells contain black iron oxide; and the 100 mg capsule shells contain FD&C Blue #1, D&C Red #28, FD&C Red #40, and red iron oxide. The capsules are printed with edible ink containing shellac, dehydrated alcohol, isopropyl alcohol, butyl alcohol, propylene glycol, strong ammonia solution, black iron oxide, and potassium hydroxide.
Distributed by:
Aurobindo Pharma USA, Inc.
279 Princeton-Hightstown Road
East Windsor, NJ 08520
Manufactured by:
Aurobindo Pharma Limited
Hyderabad-500 032, India

This Patient Information has been approved by the U.S. Food and Drug Administration
Revised: 04/2025

Storage

Store at 20° to 25°C (68° to 77°F); excursions permitted to 15° to 30°C (59° to 86°F) [see USP Controlled Room Temperature]. Protect from light, moisture, and excessive heat. Dispense in a tight, light-resistant container as defined in the USP.